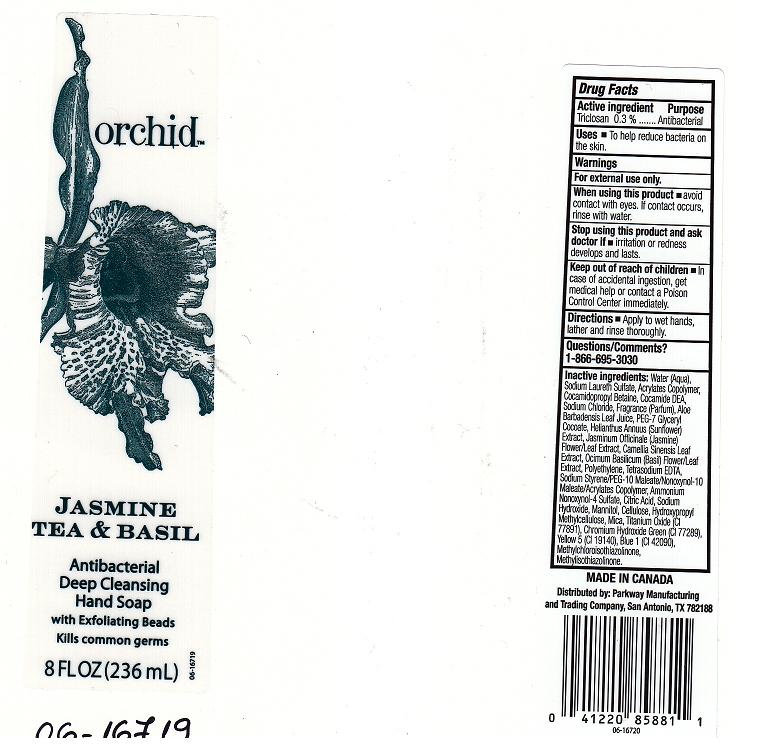 DRUG LABEL: JASMINE TEA AND BASIL ANTIBACTERIAL HAND SP
NDC: 37808-290 | Form: LIQUID
Manufacturer: HEB
Category: otc | Type: HUMAN OTC DRUG LABEL
Date: 20101223

ACTIVE INGREDIENTS: TRICLOSAN 0.3 mL/100 mL
INACTIVE INGREDIENTS: WATER; SODIUM LAURETH SULFATE; CARBOMER COPOLYMER TYPE A; COCAMIDOPROPYL BETAINE; COCO DIETHANOLAMIDE; SODIUM CHLORIDE; ALOE VERA LEAF; GLYCERYL COCOATE; SUNFLOWER SEED; JASMINUM OFFICINALE FLOWER; GREEN TEA LEAF; BASIL; LOW DENSITY POLYETHYLENE; EDETATE SODIUM; NONOXYNOL-10; AMMONIUM NONOXYNOL-4 SULFATE; ANHYDROUS CITRIC ACID; SODIUM HYDROXIDE; MANNITOL; CELLULOSE, MICROCRYSTALLINE; HYPROMELLOSES; MICA; TITANIUM DIOXIDE; CHROMIC OXIDE; FD&C YELLOW NO. 5; FD&C BLUE NO. 1; METHYLCHLOROISOTHIAZOLINONE; METHYLISOTHIAZOLINONE

DRUG FACTS

ACTIVE INGREDIENT

TRICLOSAN 0.3 PERCENT

PURPOSE

ANTIBACTERIAL

USES

TO HELP REDUCE BACTERIA ON THE SKIN.

WARNINGS

FOR EXTERNAL USE ONLY.

WHEN USING THIS PRODUCT

AVOID CONTACT WITH EYES.IF CONTACT OCCURS, RINSE WITH WATER.

STOP USING THIS PRODUCT AND ASK DOCTOR IF

IRRITATION OR REDNESS DEVELOPS AND LASTS.

KEEP OUT OF REACH OF CHILDREN

IN CASE OF ACCIDENTAL INGESTION, GET MEDICAL HELP OR CONTACT A POISON CONTROL CENTER IMMEDIATELY.

DIRECTIONS

APPLY TO WET HANDS, LATHER AND RINSE THOROUGHLY.

QUESTIONS OR COMMENTS

1-866-695-3030

INACTIVE INGREDIENTS

WATER, SODIUM LAURETH SULFATE, ACRYLATES COPOLYMER, COCAMIDOPROPYL BETAINE, COCAMIDE DEA, SODIUM CHLORIDE, FRAGRANCE (PARFUM), ALOE BARBADENSIS LEAF JUICE, PEG-7 GLYCERYL COCOATE, HELIANTHUS ANNUUS (SUNFLOWER) EXTRACT, JASMINUM OFFICINALE (JASMINE) FLOWER/LEAF EXTRACT, CAMELLIA SINENSIS LEAF EXTRACT, OCIMUM BASILICUM (BASIL) FLOWER/LEAF EXTRACT, TETRASODIUM EDTA, SODIUM STYRENE/PEG-10 MALEATE/NONOXYNOL-10 MALEATE/ACRYLATES COPOLYMER, AMMONIUM NONOXYNOL-4 SULFATE, CITRIC ACID, SODIUM HYDROXIDE, MANNITOL, CELLULOSE, HYDROXYPROPYL METHYLCELLULOSE, MICA, TITANIUM OXIDE (CI 77891), CHROMIUM HYDROXIDE GREEN (CI 77289), YELLOW 5 (CI 19140), BLUE 1 (CI 42090), METHYLCHLOROISOTHIAZOLINONE, METHYLISOTHIAZOLINONE.